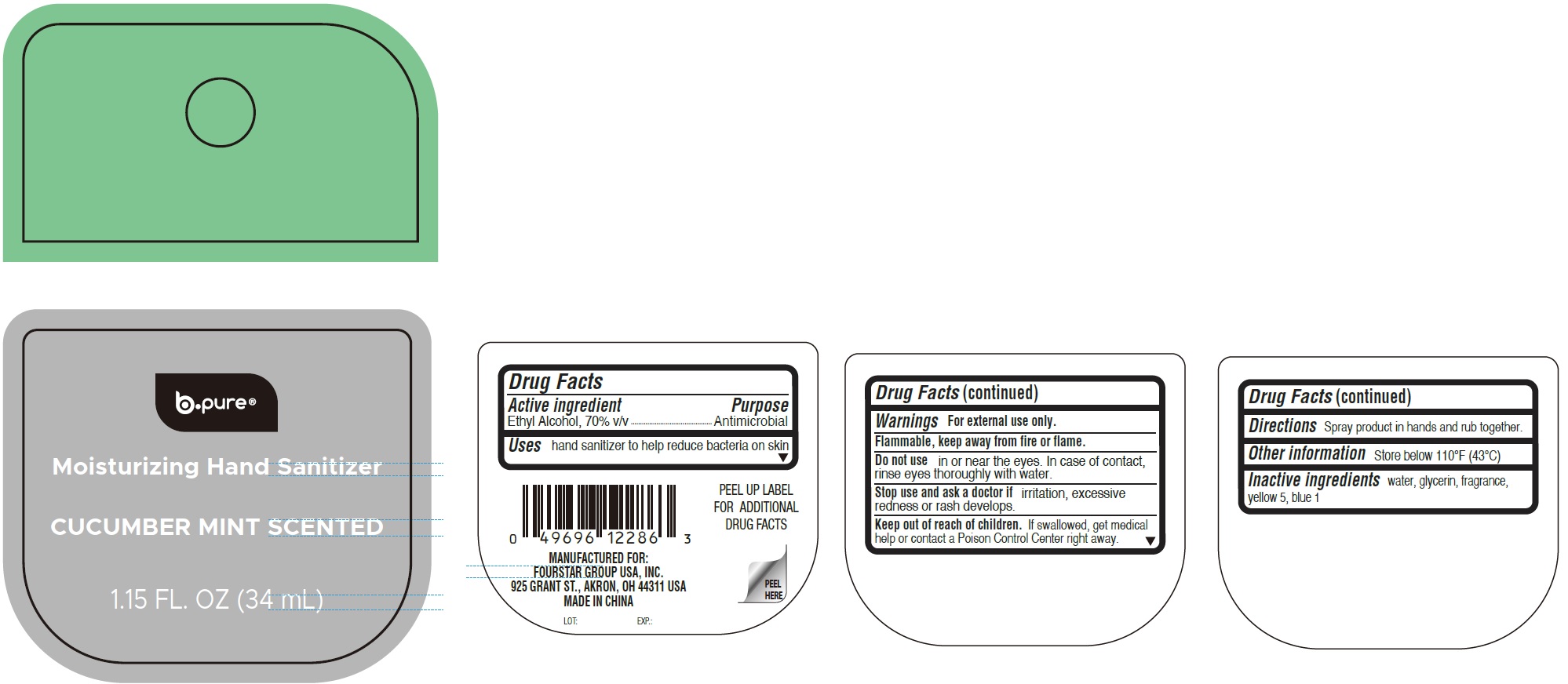 DRUG LABEL: B Pure Moisturizing Hand Sanitizer Cucumber Mint Scented
NDC: 80684-127 | Form: LIQUID
Manufacturer: Fourstar Group USA, Inc
Category: otc | Type: HUMAN OTC DRUG LABEL
Date: 20260202

ACTIVE INGREDIENTS: ALCOHOL 70 mL/100 mL
INACTIVE INGREDIENTS: GLYCERIN; WATER; FD&C YELLOW NO. 5; FD&C BLUE NO. 1

B-Pure Moisturizing Hand Sanitizer, Cucumber Mint Scented

Active ingredient

Ethyl Alcohol, 70% v/v

Purpose

Antimicrobial

Uses

hand sanitizer to help reduce bacteria on skin

Warnings

For external use only.

Flammable, keep away from fire or flame.

Do not use

in or near the eyes. In case of contact, rinse eyes thoroughly with water.

Stop use and ask a doctor if

irritation, excessive redness or rash develops.

Keep out of reach of children.

If swallowed, get medical help or contact a Poison Control Center right away.

Directions

Spray product in hands and rub together.

Other information

Store below 110°F (43°C)

Inactive ingredients

water, glycerin, fragrance, yellow 5, blue 1